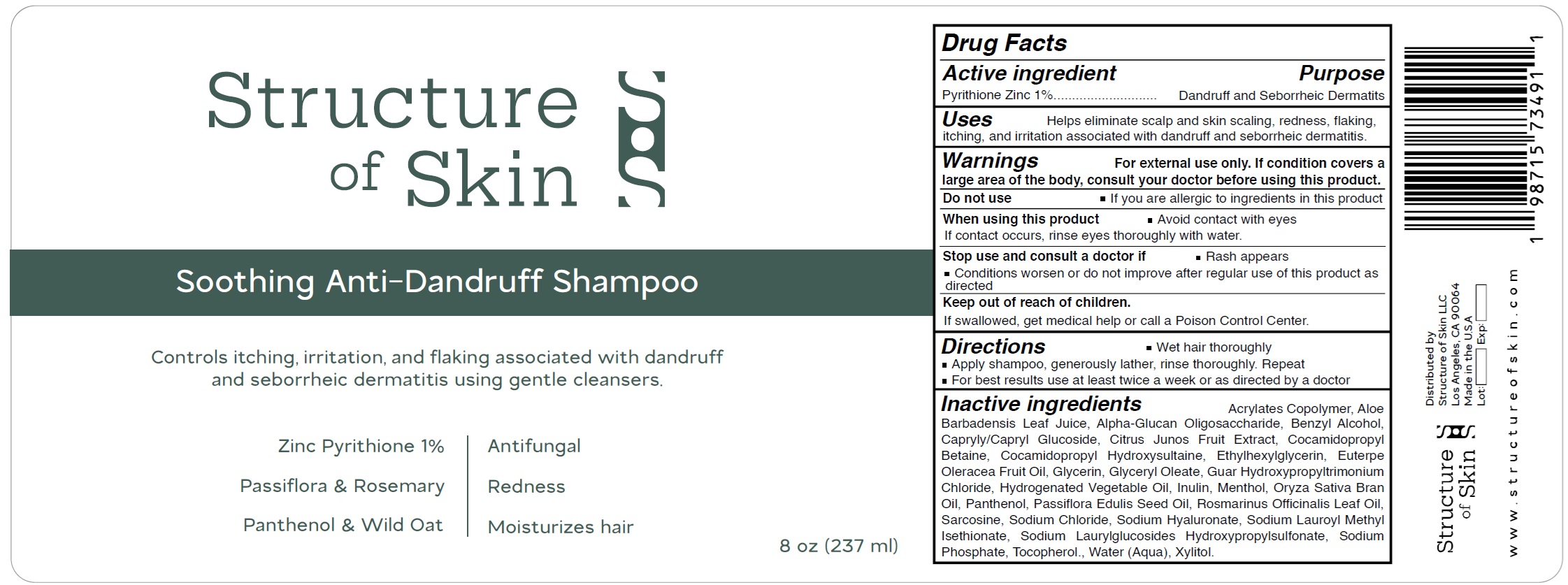 DRUG LABEL: Structure of Skin Soothing Anti-Dandruff
NDC: 85567-323 | Form: SHAMPOO
Manufacturer: STRUCTURE OF SKIN LLC
Category: otc | Type: HUMAN OTC DRUG LABEL
Date: 20250418

ACTIVE INGREDIENTS: PYRITHIONE ZINC 10 mg/1 mL
INACTIVE INGREDIENTS: ALOE VERA LEAF JUICE; .ALPHA.-GLUCAN OLIGOSACCHARIDE; BENZYL ALCOHOL; CAPRYLYL/CAPRYL OLIGOGLUCOSIDE; CITRUS JUNOS FRUIT; COCAMIDOPROPYL BETAINE; COCAMIDOPROPYL HYDROXYSULTAINE; ETHYLHEXYLGLYCERIN; ACAI OIL; GLYCERIN; GLYCERYL OLEATE; GUAR HYDROXYPROPYLTRIMONIUM CHLORIDE; INULIN; MENTHOL; RICE BRAN OIL; PANTHENOL; PASSIFLORA EDULIS SEED OIL; ROSEMARY OIL; SARCOSINE; SODIUM CHLORIDE; HYALURONATE SODIUM; SODIUM LAUROYL METHYL ISETHIONATE; SODIUM LAURYLGLUCOSIDES HYDROXYPROPYLSULFONATE; SODIUM PHOSPHATE; TOCOPHEROL; WATER; XYLITOL

Structure of Skin Soothing Anti-Dandruff Shampoo

Active ingredient

Pyrithione Zinc 1%

Purpose

Dandruff and Seborrheic Dermatits

Uses

Helps eliminate scalp and skin scaling, redness, flaking, itching, and irritation associated with dandruff and seborrheic dermatitis.

Warnings

For external use only. If condition covers a large area of the body, consult your doctor before using this product.

Do not use

- If you are allergic to ingredients in this product

When using this product

- Avoid contact with eyes If contact occurs, rinse eyes thoroughly with water.

Stop use and consult a doctor if

- Rash appears
- Conditions worsen or do not improve after regular use of this product as directed

Keep out of reach of children.

If swallowed, get medical help or call a Poison Control Center.

Directions

- Wet hair thoroughly
- Apply shampoo, generously lather, rinse thoroughly. Repeat
- For best results use at least twice a week or as directed by a doctor

Inactive ingredients

Acrylates Copolymer, Aloe Barbadensis Leaf Juice, Alpha-Glucan Oligosaccharide, Benzyl Alcohol, Capryly/Capryl Glucoside, Citrus Junos Fruit Extract, Cocamidopropyl Betaine, Cocamidopropyl Hydroxysultaine, Ethylhexylglycerin, Euterpe Oleracea Fruit Oil, Glycerin, Glyceryl Oleate, Guar Hydroxypropyltrimonium Chloride, Hydrogenated Vegetable Oil, Inulin, Menthol, Oryza Sativa Bran Oil, Panthenol, Passiflora Edulis Seed Oil, Rosmarinus Officinalis Leaf Oil, Sarcosine, Sodium Chloride, Sodium Hyaluronate, Sodium Lauroyl Methyl Isethionate, Sodium Laurylglucosides Hydroxypropylsulfonate, Sodium Phosphate, Tocopherol., Water (Aqua), Xylitol.